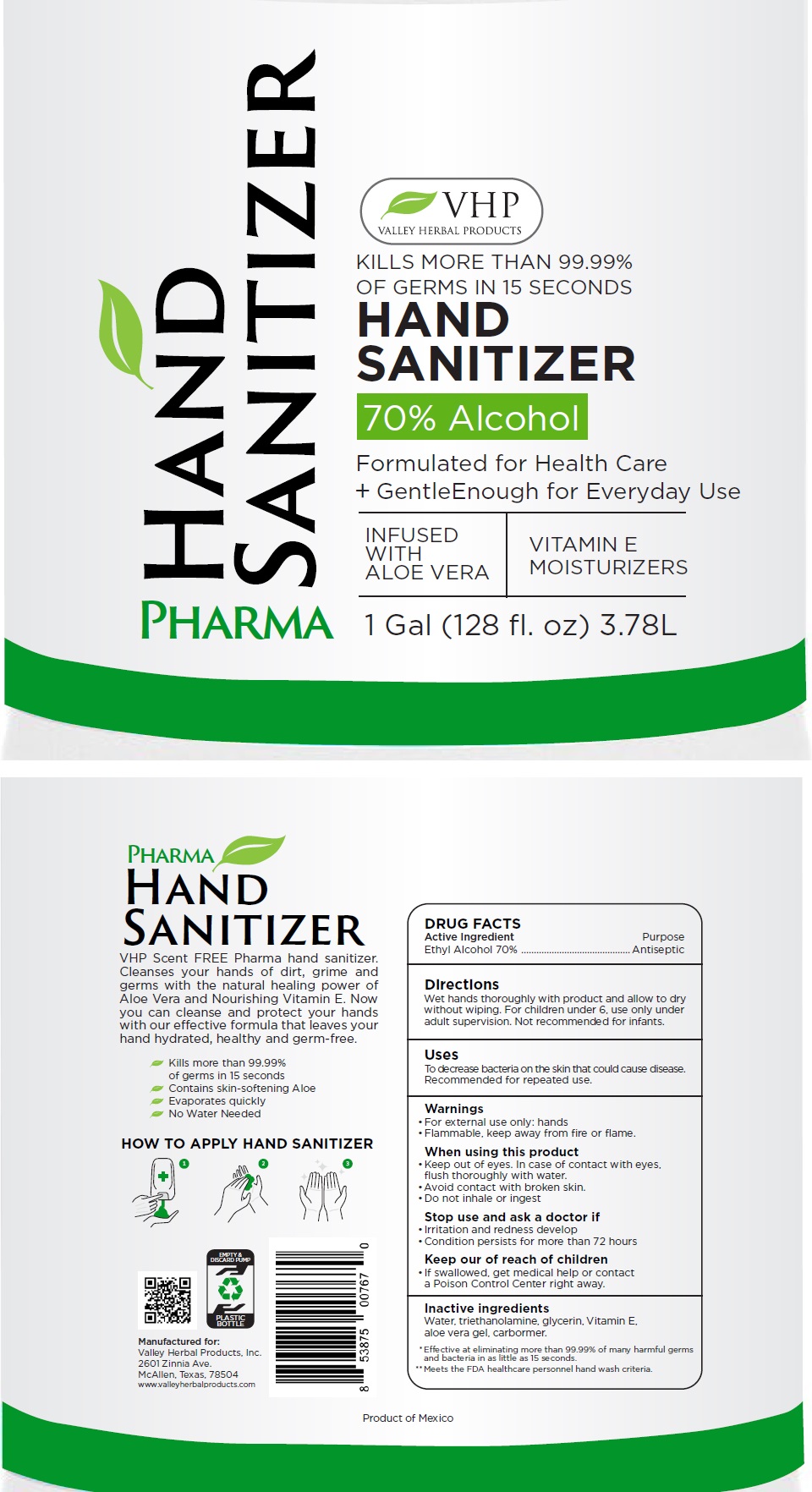 DRUG LABEL: VHP HAND SANITIZER
NDC: 75653-100 | Form: LIQUID
Manufacturer: Valley Herbal Products, Inc.
Category: otc | Type: HUMAN OTC DRUG LABEL
Date: 20200518

ACTIVE INGREDIENTS: ALCOHOL 70 L/100 L
INACTIVE INGREDIENTS: WATER; TROLAMINE; GLYCERIN; .ALPHA.-TOCOPHEROL; ALOE VERA LEAF; CARBOMER HOMOPOLYMER, UNSPECIFIED TYPE

VHP HAND SANITIZER

Active Ingredient

Ethyl Alcohol 70%

Purpose

Antiseptic

Directions

Wet hands thoroughly with product and allow to dry without wiping. For children under 6, use only under adult supervision. Not recommended for infants.

Uses

To decrease bacteria on the skin that could cause disease. Recommended for repeated use.

Warnings

• For external use only: hands.

• Flammable, keep away from fire or flame.

When using this product

• keep out of eyes. In case of contact with eyes, flush thoroughly with water.

• Avoid contact with broken skin.

• Do not inhale or ingest

Stop use and ask a doctor if

▪ Irritation and redness develop

▪ Condition persists for more than 72 hours

Keep out of reach of children

• If swallowed, get medical help or contact a Poison Control Center right away.

Inactive Ingredients

Water, triethanolamine, glycerin, Vitamin E, aloe vera gel, carbomer.

PHARMA

VALLEY HERBAL PRODUCTS

KILLS MORE THAN 99.99% OF GERMS IN 15 SECONDS

Formulated for Health Care

+ Gentle Enough for Everyday Use

INFUSED WITH ALOE VERA

VITAMIN E MOISTURIZERS

VHP Scent FREE Pharma hand sanitizer. Cleanses your hands of dirt, grime and germs with the natural healing power of Aloe Vera and Nourishing Vitamin E. Now you can cleanse and protect your hands with our effective formula that leaves your hand hydrated, healthy and germ-free.

• Kills more than 99.99% of germs in 15 seconds

• Contains skin-softening Aloe

• Evaporates quickly

• No water needed

HOW TO APPLY HAND SANITIZER

Manufactured for:

Valley Herbal Products, Inc.

2601 zinnia Ave.

McAllen, Texas, 78504

www.valleyherbalproducts.com

* Effective at eliminating more than 99.99% of many harmful germs and bacteria in as little as 15 seconds.

** Meets the FDA healthcare personnel hand wash criteria

Product of Mexico